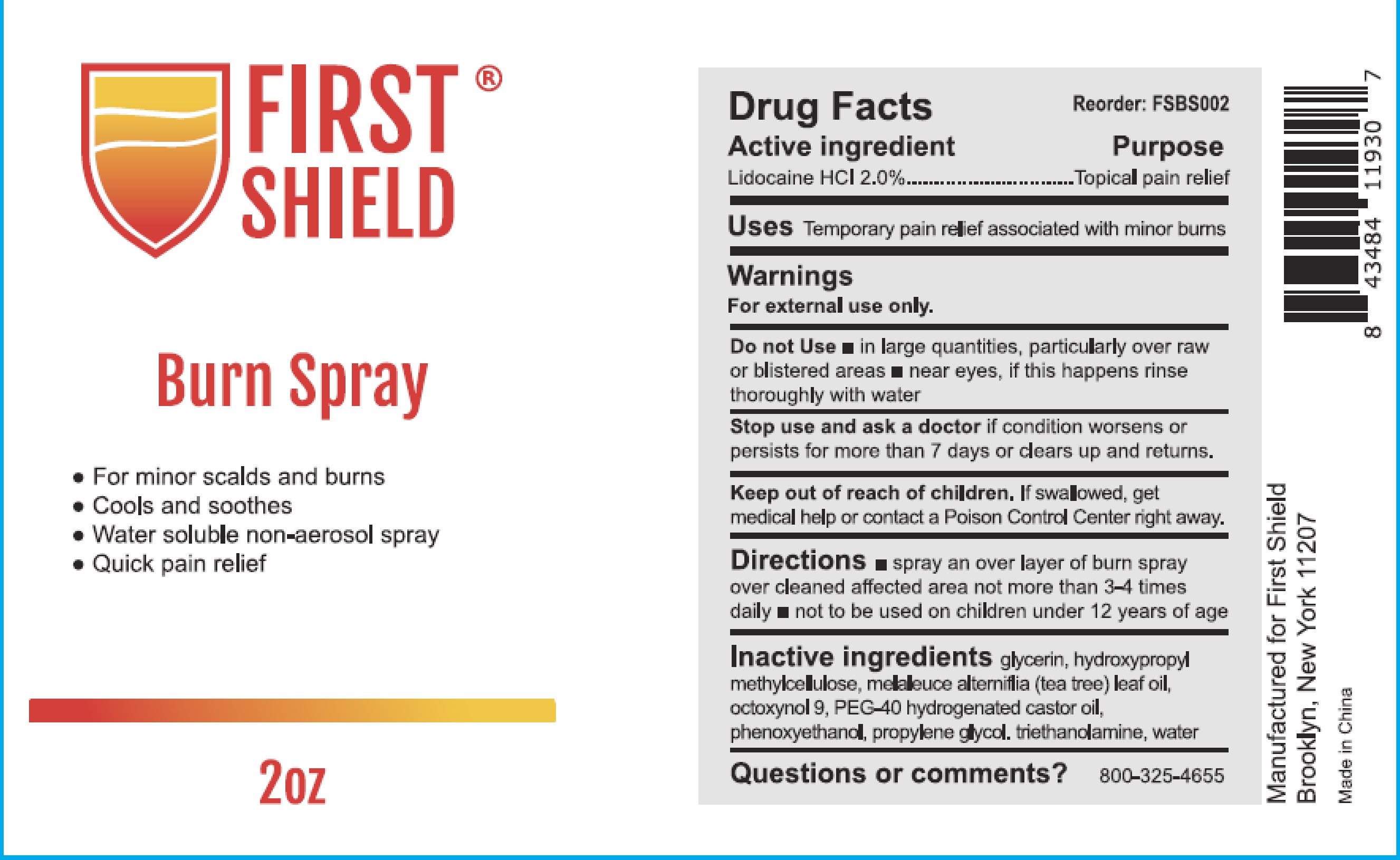 DRUG LABEL: FIRST SHIELD
NDC: 72976-004 | Form: SPRAY
Manufacturer: Ever Ready First Aid
Category: otc | Type: HUMAN OTC DRUG LABEL
Date: 20240115

ACTIVE INGREDIENTS: LIDOCAINE HYDROCHLORIDE 20 mg/1 mL
INACTIVE INGREDIENTS: PHENOXYETHANOL; WATER; GLYCERIN; TEA TREE OIL; HYPROMELLOSES; PROPYLENE GLYCOL; TROLAMINE; OCTOXYNOL 9; POLYOXYL 40 HYDROGENATED CASTOR OIL

72976-004 FIRST SHIELD
Burn Spray

Active ingredient

Lidocaine HCI 2.0%

Purpose

Topical pain relief

Uses

Temporary pain relief associated with minor burns

Warnings

For external use only.

Do not use

- in large quantities, particularly over raw or blistered areas
- near eyes, if this happens rinse thoroughly with water

Stop use and ask a doctor if condition worsens or persists for more than 7 days or clears up and returns.

Keep out of reach of children. If swallowed, get medical help or contact a Poison Control Center right away.

Directions

- spray an over layer of burn spray over cleaned affected area not more than 3-4 times daily
- not to be used on children under 12 years of age

INACTIVE INGREDIENT

Inactive ingredients glycerin, hydroxypropyl methylcllulose, melaleuce alterniflia (tea tree) leaf oil, octoxynol 9,PEEG-40 hydrogenated castor oil, phenoxyethanol, propylene glycol, triethanolamine, water

Questions or comments？ 800-325-4655